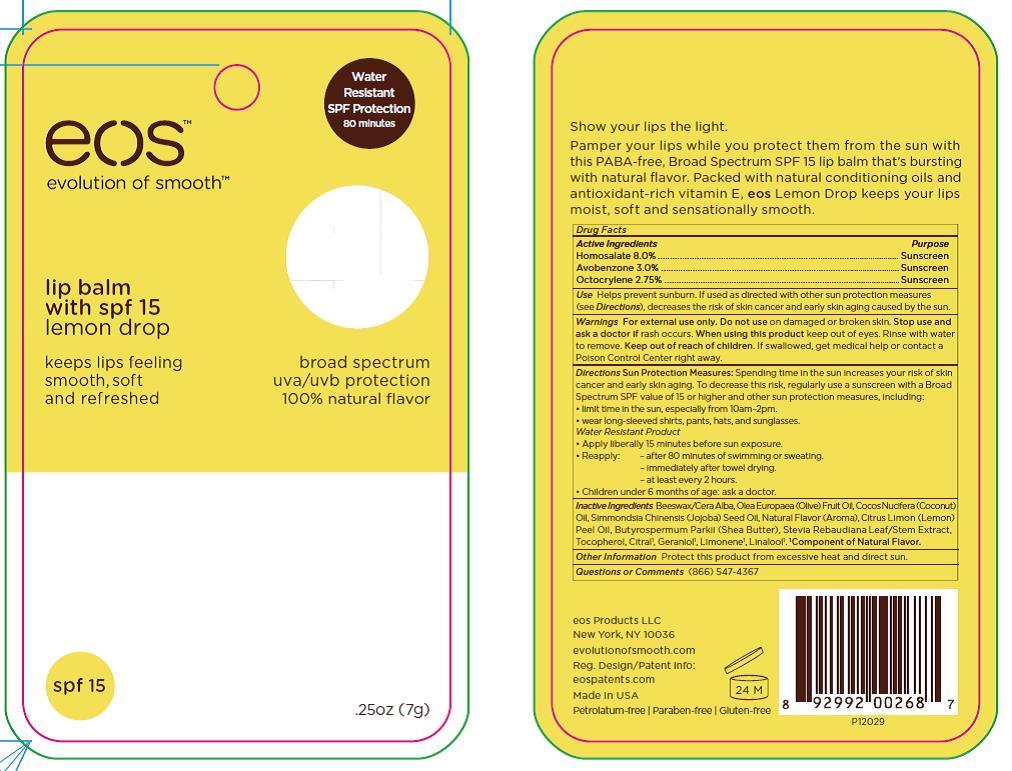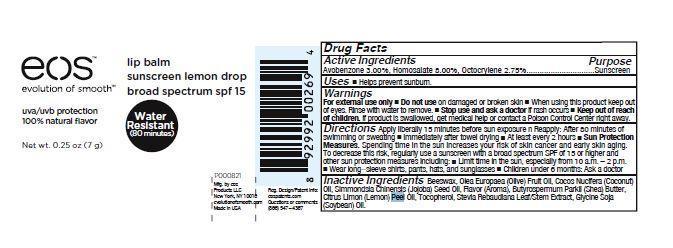 DRUG LABEL: eos lip balm sunscreen broad spectrum spf 15
NDC: 70170-0001 | Form: STICK
Manufacturer: eos Products LLC
Category: otc | Type: HUMAN OTC DRUG LABEL
Date: 20151105

ACTIVE INGREDIENTS: AVOBENZONE 0.21 g/7 g; HOMOSALATE 0.56 g/7 g; OCTOCRYLENE 0.20 g/7 g
INACTIVE INGREDIENTS: COCONUT OIL; OLIVE OIL; YELLOW WAX; JOJOBA OIL; SHEA BUTTER; TOCOPHEROL; SOYBEAN OIL; LEMON; LEMON OIL; STEVIA REBAUDIUNA LEAF

eos lip balm sunscreen broad spectrum spf 15

Drug Facts

Active Ingredients Purpose

Avobenzone 3.0% Sunscreen

Homosalate 8.0% Sunscreen

Octocrylene 2.75% Sunscreen

Use

Helps prevent sunburn. If used as directed with other sun protection measures (see Directions), decreases the risk of skin cancer and early skin aging caused by the sun.

Warnings

For external use only

Do not use on damaged or broken skin.

When using this product keep out of eyes. Rinse with water to remove.

Stop use and ask a doctor if rash occurs.

Keep out of reach of children.

If swallowed, get medical help or contact a Poison Control Center right away.

Directions

• Apply liberally 15 minutes before sun exposure.
• Reapply: – after 80 minutes of swimming or sweating.
– immediately after towel drying.
– at least every 2 hours.

Sun Protection Measures: Spending time in the sun increases your risk of skin cancer and early skin aging. To decrease this risk, regularly use a sunscreen with a Broad Spectrum SPF value of 15 or higher and other sun protection measures, including:
• limit time in the sun, especially from 10am–2pm.
• wear long-sleeved shirts, pants, hats, and sunglasses.

Inactive ingredients

Beeswax, Olea Europaea (Olive) Fruit Oil, Cocos Nucifera (Coconut) Oil, Simmondsia Chinensis (Jojoba) Seed Oil, Flavor (Aroma), Butyrospermum Parkii (Shea) Butter, Citrus Limon (Lemon) Peel Oil, Tocopherol, Stevia Rebaudiana Leaf/Stem Extract, Glycine Soja (Soybean) Oil.

Other information

Protect this product from excessive heat and direct sun.

Questions or Comments

(866) 547-4367

Principle Display Panel - 0.25 oz BLISTER PACK

eos

lip balm Lemon drop

sunscreen broad spectrum spf 15

Water Resistant (80 minutes)

Net wt. 0.25 oz (7 g)

Principle Display Panel - 0.25 oz CELLO PACK

eos

lip balm Lemon drop

sunscreen broad spectrum spf 15

Water Resistant (80 minutes)

Net wt. 0.25 oz (7 g)

ASK DOCTOR

• Children under 6 months of age: ask a doctor.